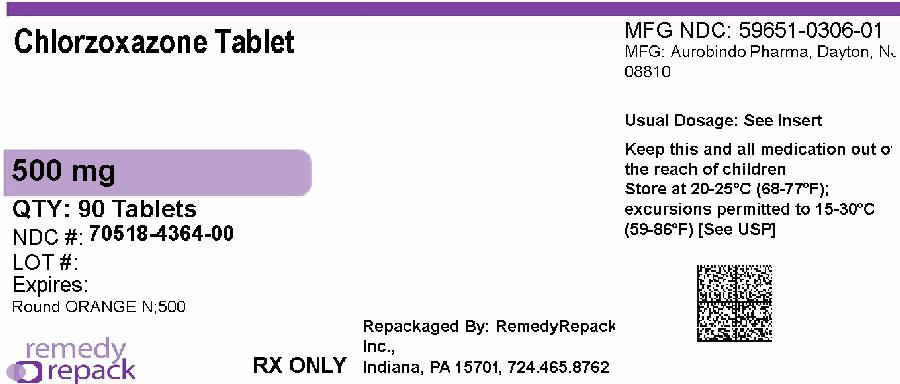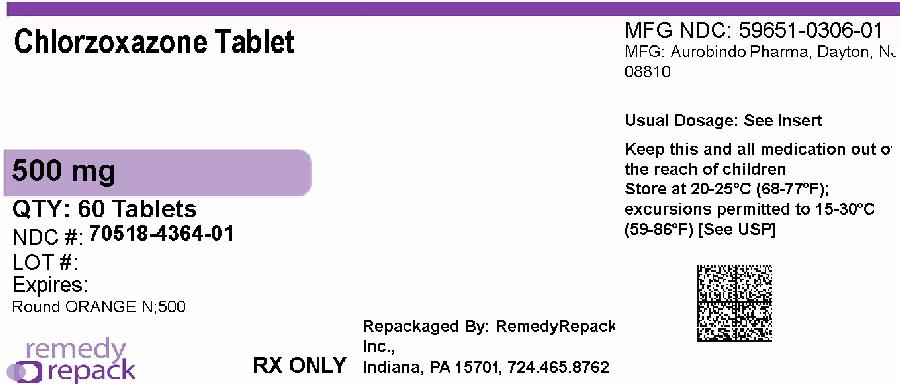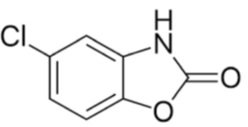 DRUG LABEL: CHLORZOXAZONE
NDC: 70518-4364 | Form: TABLET
Manufacturer: REMEDYREPACK INC.
Category: prescription | Type: HUMAN PRESCRIPTION DRUG LABEL
Date: 20260129

ACTIVE INGREDIENTS: CHLORZOXAZONE 500 mg/1 1
INACTIVE INGREDIENTS: FD&C YELLOW NO. 6; D&C RED NO. 27; HYPROMELLOSE 2910 (3 MPA.S); LACTOSE MONOHYDRATE; MAGNESIUM STEARATE; MICROCRYSTALLINE CELLULOSE; POLYSORBATE 80; STARCH, CORN; SODIUM STARCH GLYCOLATE TYPE A POTATO

Chlorzoxazone Tablets, USP

For Painful Musculoskeletal Conditions

PRESCRIBING INFORMATION

DESCRIPTION

Each 375 mg chlorzoxazone tablet contains: Chlorzoxazone USP 375 mg.

Each 500 mg chlorzoxazone tablet contains: Chlorzoxazone USP 500 mg.

Each 750 mg chlorzoxazone tablet contains: Chlorzoxazone USP 750 mg.

Chemical Name: 5-Chloro-2-benzoxazolinone.

Structural Formula:

Molecular Formula: C7H4ClNO2

Molecular Weight: 169.56

Chlorzoxazone, USP is a white or practically white, practically odorless, crystalline powder. Chlorzoxazone USP is slightly soluble in water; sparingly soluble in alcohol, in isopropyl alcohol, and in methanol; soluble in solutions of alkali hydroxides and ammonia.

Inactive ingredients:

375 mg contains colloidal silicon dioxide, corn starch, croscarmellose sodium, docusate sodium with sodium benzoate, lactose monohydrate, magnesium stearate and microcrystalline cellulose.

500 mg contains D&C Red 27/Phloxine Aluminium lake, FD&C Yellow 6/Sunset Yellow FCF Aluminium lake, hypromellose, lactose monohydrate, magnesium stearate, microcrystalline cellulose, polysorbate 80, pregelatinized starch, sodium starch glycolate.

750 mg contains colloidal silicon dioxide, corn starch, croscarmellose sodium, docusate sodium with sodium benzoate, lactose monohydrate, magnesium stearate and microcrystalline cellulose.
Meets USP dissolution test 5 for 500 mg.
FDA approved dissolution method differs from that of the USP for 375 mg and 750 mg.

CLINICAL PHARMACOLOGY

Chlorzoxazone is a centrally-acting agent for painful musculoskeletal conditions. Data available from animal experiments as well as human study indicate that chlorzoxazone acts primarily at the level of the spinal cord and subcortical areas of the brain where it inhibits multisynaptic reflex arcs involved in producing and maintaining skeletal muscle spasm of varied etiology. The clinical result is a reduction of the skeletal muscle spasm with relief of pain and increased mobility of the involved muscles. Blood levels of chlorzoxazone can be detected in people during the first 30 minutes and peak levels may be reached, in the majority of the subjects, in about 1 to 2 hours after oral administration of chlorzoxazone. Chlorzoxazone is rapidly metabolized and is excreted in the urine, primarily in a conjugated form as the glucuronide. Less than one percent of a dose of chlorzoxazone is excreted unchanged in the urine in 24 hours.

INDICATIONS AND USAGE

Chlorzoxazone is indicated as an adjunct to rest, physical therapy, and other measures for the relief of discomfort associated with acute, painful musculoskeletal conditions. The mode of action of this drug has not been clearly identified, but may be related to its sedative properties. Chlorzoxazone does not directly relax tense skeletal muscles in man.

CONTRAINDICATIONS

Chlorzoxazone is contraindicated in patients with known intolerance to the drug.

WARNINGS

Serious (including fatal) hepatocellular toxicity has been reported rarely in patients receiving chlorzoxazone. The mechanism is unknown but appears to be idiosyncratic and unpredictable. Factors predisposing patients to this rare event are not known. Patients should be instructed to report early signs and/or symptoms of hepatotoxicity such as fever, rash, anorexia, nausea, vomiting, fatigue, right upper quadrant pain, dark urine, or jaundice. Chlorzoxazone should be discontinued immediately and a physician consulted if any of these signs or symptoms develop. Chlorzoxazone use should also be discontinued if a patient develops abnormal liver enzymes (e.g., AST, ALT, alkaline phosphatase and bilirubin.)

The concomitant use of alcohol or other central nervous system depressants may have an additive effect.

Usage in Pregnancy:

The safe use of chlorzoxazone has not been established with respect to the possible adverse effects upon fetal development. Therefore, it should be used in women of childbearing potential only when, in the judgment of the physician, the potential benefits outweigh the possible risks.

PRECAUTIONS

Chlorzoxazone should be used with caution in patients with known allergies or with a history of allergic reactions to drugs. If a sensitivity reaction occurs such as urticaria, redness, or itching of the skin, the drug should be stopped.

If any symptoms suggestive of liver dysfunction are observed, the drug should be discontinued.

ADVERSE REACTIONS

Chlorzoxazone containing products are usually well tolerated. It is possible in rare instances that chlorzoxazone may have been associated with gastrointestinal bleeding. Drowsiness, dizziness, lightheadedness, malaise, or over-stimulation may be noted by an occasional patient. Rarely, allergic type skin rashes, petechiae, or ecchymoses may develop during treatment. Angioneurotic edema or anaphylactic reactions are extremely rare. There is no evidence that the drug will cause renal damage. Rarely, a patient may note discoloration of the urine resulting from a phenolic metabolite of chlorzoxazone. This finding is of no known clinical significance.

To report SUSPECTED ADVERSE EVENTS, contact Aurobindo Pharma USA, Inc. at 1-866-850-2876 or FDA at 1-800- FDA-1088 or http://www.fda.gov/ for voluntary reporting of adverse reactions.

OVERDOSAGE

Symptoms:Initially, gastrointestinal disturbances such as nausea, vomiting, or diarrhea together with drowsiness, dizziness, lightheadedness or headache may occur. Early in the course there may be malaise or sluggishness followed by marked loss of muscle tone, making voluntary movement impossible. The deep tendon reflexes may be decreased or absent. The sensorium remains intact, and there is no peripheral loss of sensation. Respiratory depression may occur with rapid, irregular respiration and intercostal and substernal retraction. The blood pressure is lowered, but shock has not been observed.

Treatment:Gastric lavage or induction of emesis should be carried out, followed by administration of activated charcoal. Thereafter, treatment is entirely supportive. If respirations are depressed, oxygen and artificial respiration should be employed and a patent airway assured by use of an oropharyngeal airway or endotracheal tube. Hypotension may be counteracted by use of dextran, plasma, concentrated albumin or a vasopressor agent such as norepinephrine. Cholinergic drugs or analeptic drugs are of no value and should not be used.

DOSAGE AND ADMINISTRATION

Usual Adult Dosage

Chlorzoxazone tablets USP, 375 mg:

One tablet three or four times daily. If adequate response is not obtained with this dose, the 375 mg tablets may be increased to two tablets (750 mg) three or four times daily. As improvement occurs dosage can usually be reduced.

Chlorzoxazone tablets USP, 500 mg:

One tablet three or four times daily. If adequate response is not obtained with this dose, it may be increased to one and one-half tablets (750 mg) three or four times daily. As improvement occurs dosage can usually be reduced.

Chlorzoxazone tablets USP, 750 mg:

1/3 tablet (250 mg) three or four times daily. Initial dosage for painful musculoskeletal conditions should be 2/3 tablet (500 mg) three or four times daily. If adequate response is not obtained with this dose, it may be increased to one tablet (750 mg) three or four times daily. As improvement occurs dosage can usually be reduced.

HOW SUPPLIED

Chlorzoxazone tablets USP are supplied as follows:

500 mg

A light orange to orange round shaped, flat hexagonal, beveled debossed with “N” on one side of break line and “500” on other side of break line and plain on other side.

NDC: 70518-4364-00

NDC: 70518-4364-01

PACKAGING: 90 in 1 BOTTLE PLASTIC

PACKAGING: 60 in 1 BOTTLE PLASTIC

Dispense in tight container as defined in the official compendium.

Store at 20° to 25° C (68° to 77° F) [see USP Controlled Room Temperature].

Repackaged and Distributed By:

Remedy Repack, Inc.

625 Kolter Dr. Suite #4 Indiana, PA 1-724-465-8762

PACKAGE LABEL

DRUG: CHLORZOXAZONE

GENERIC: CHLORZOXAZONE

DOSAGE: TABLET

ADMINSTRATION: ORAL

NDC: 70518-4364-0

NDC: 70518-4364-1

COLOR: orange

SHAPE: ROUND

SCORE: Two even pieces

SIZE: 13 mm

IMPRINT: N;500

PACKAGING: 90 in 1 BOTTLE, PLASTIC

PACKAGING: 60 in 1 BOTTLE, PLASTIC

ACTIVE INGREDIENT(S):

- CHLORZOXAZONE 500mg in 1

INACTIVE INGREDIENT(S):

- D&C RED NO. 27
- FD&C YELLOW NO. 6
- HYPROMELLOSE 2910 (3 MPA.S)
- LACTOSE MONOHYDRATE
- MAGNESIUM STEARATE
- MICROCRYSTALLINE CELLULOSE
- POLYSORBATE 80
- STARCH, CORN
- SODIUM STARCH GLYCOLATE TYPE A POTATO